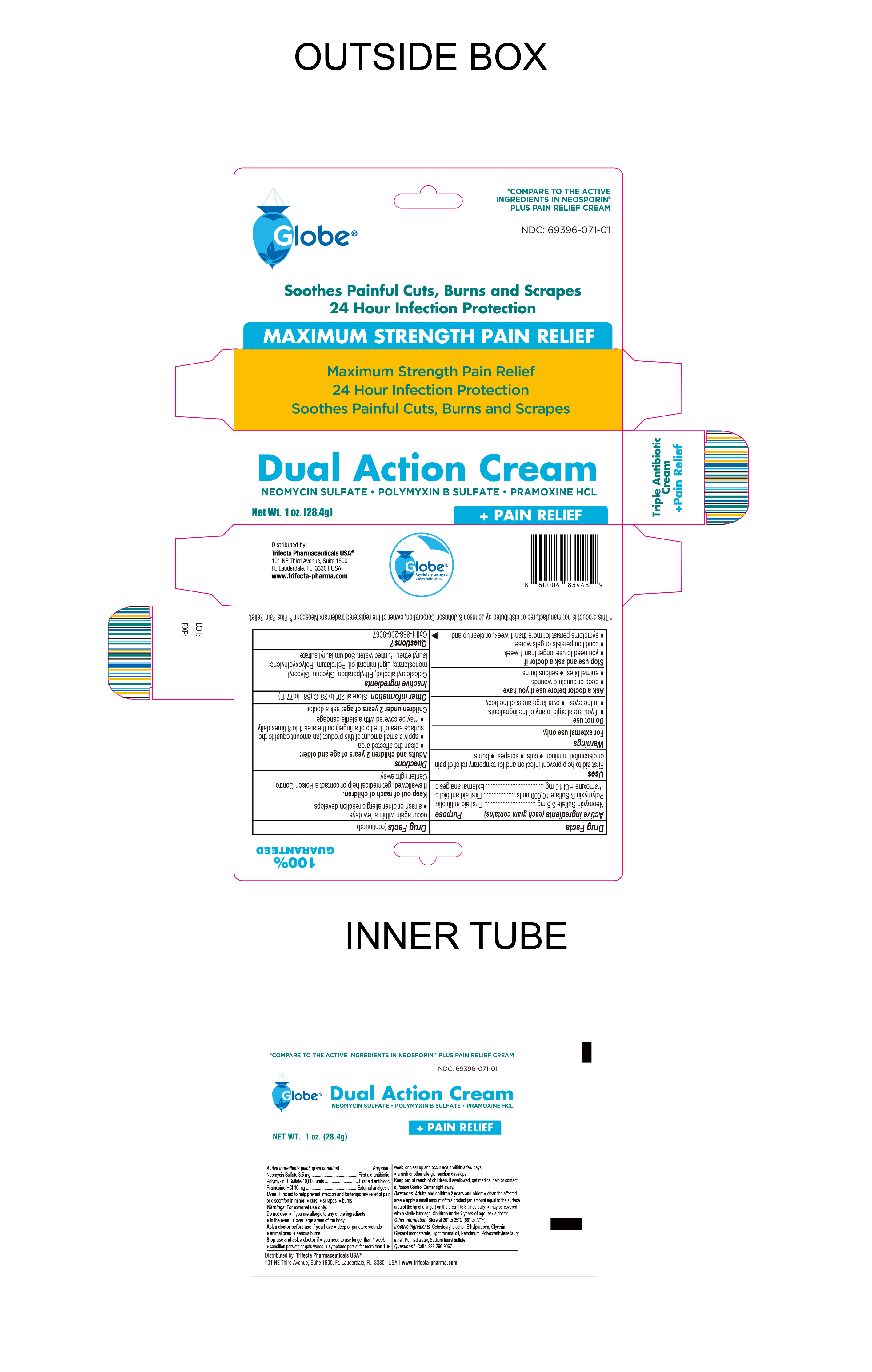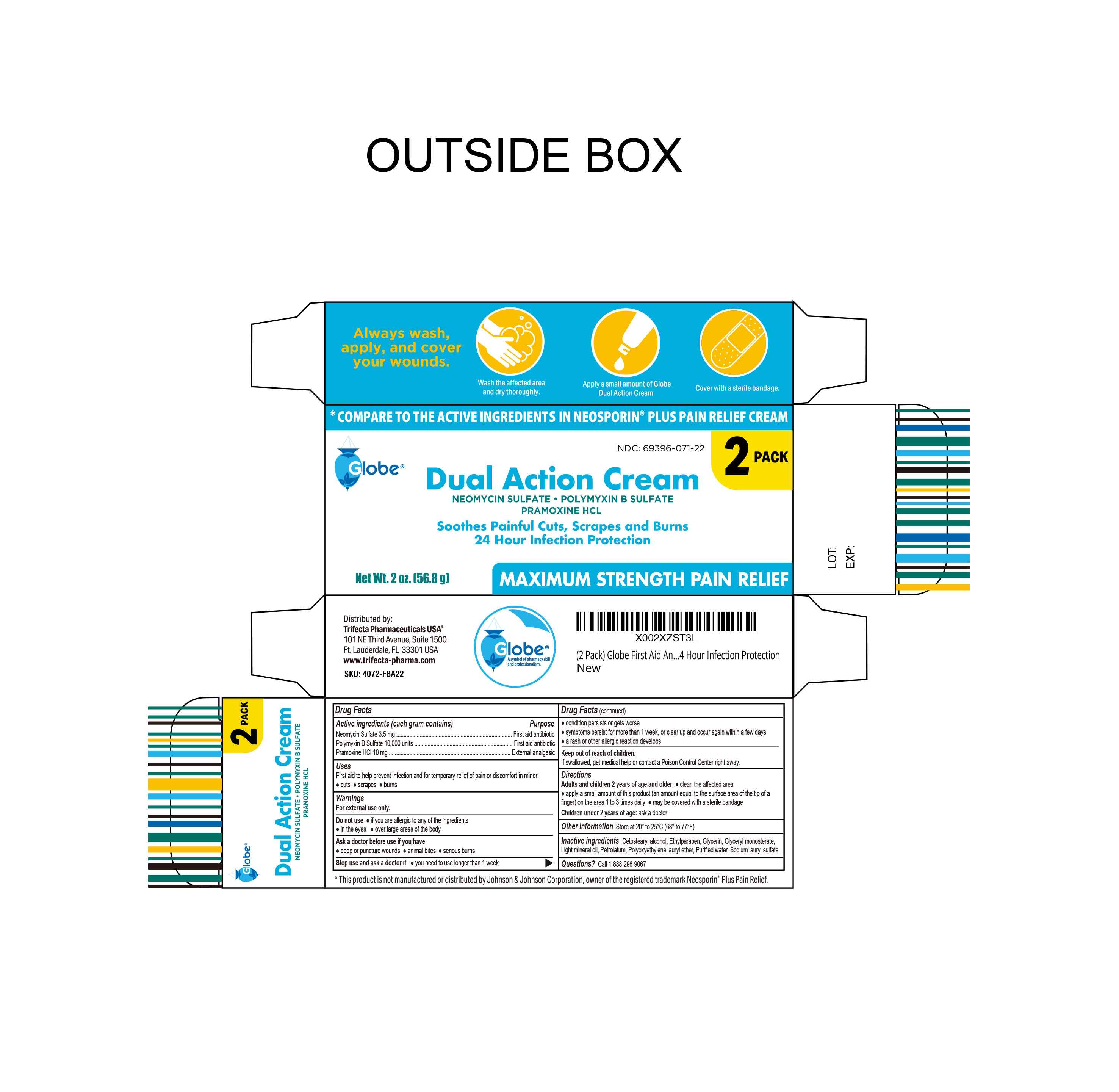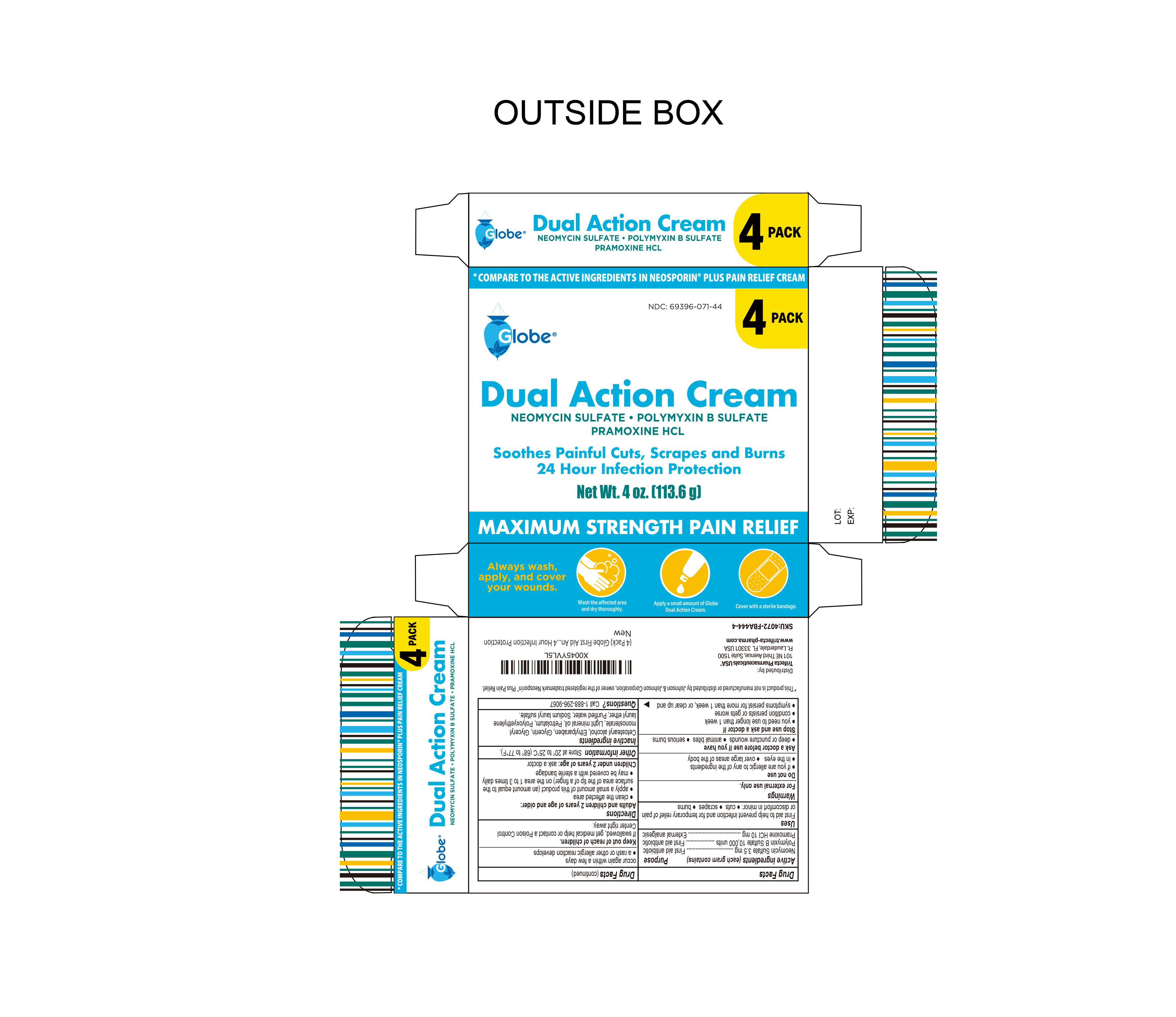 DRUG LABEL: Dual Action Cream
NDC: 69396-071 | Form: CREAM
Manufacturer: Trifecta Pharmaceutical USA LLC
Category: otc | Type: HUMAN OTC DRUG LABEL
Date: 20250823

ACTIVE INGREDIENTS: NEOMYCIN SULFATE 3.5 mg/1 g; PRAMOXINE HYDROCHLORIDE 10 mg/1 g; POLYMYXIN B SULFATE 10000 [USP'U]/1 g
INACTIVE INGREDIENTS: PETROLATUM; GLYCERYL MONOSTEARATE; LAURETH-23; ETHYLPARABEN; WATER; SODIUM LAURYL SULFATE; CETOSTEARYL ALCOHOL; GLYCERIN; LIGHT MINERAL OIL

Dual Action Cream

Active Ingredient

Neomycin 3.5mg

Purpose

First Aid Antibiotic

Active Ingredient

Polymyxin B 10,000 Units

Purpose

First Aid Antibiotic

Active Ingredient

Pramoxine HCL 10mg

Purpose

External Analgesic

Uses

First Aid to help prevent infection iand for temporary relief of pain or discomfort in minor cuts, scrapes and burns.

Warnings

For external use only. Do not use:

- If you are allergic to any of the ingredients
- in the eyes
- over large areas of the body

Ask a Doctor before Use

Ask Doctor before use if you have:

- Deep or puncture wounds
- Animal bites
- Serious burns

Stop Use and ask a Doctor if:

- Condition persists or gets worse
- You need to use longer than 1 week
- Symptoms persist for more than 1 week or clear up and occur within a few days.
- A rash or other allergive reaction develops

Keep out of Reach of Children

If swallowed, get medical help or contact a Poison Control Center right away

Directions

Adults and children 2 years of age and older

- Clean the affected area
- Apply a small amount of this product (an amount equal to the surface area of the tip of a finger) on the area 1 to 3 times daily
- May be covered with a sterile bandage

Children under 2 years of age: ask a doctor

Questions

For Questions please call 1 888 296 9067

Other Information

- Store at 20° to 25°C (68° to 77°F)

Inactive Ingredient:

Cetostearyl alcohol, Ethylparaben, Glycerin, Glyceryl monosterate, Light Mineral Oil, Petrolatum, Polyoxyethylene Lauryl Ether, Purified Water, Sodium Lauryl Sulfate.

Distributed By

Trifecta Pharmaceuticals USA

101 NE Third Avenue, Suite 1500

Ft. Lauderdale, FL. 33301

www.trifecta-pharma.com

Product of PRC

This product is not manufactured or distributed by Johnson & Johnson Corporation, owner of the registered trademark Neosporin Plus Pain Relief